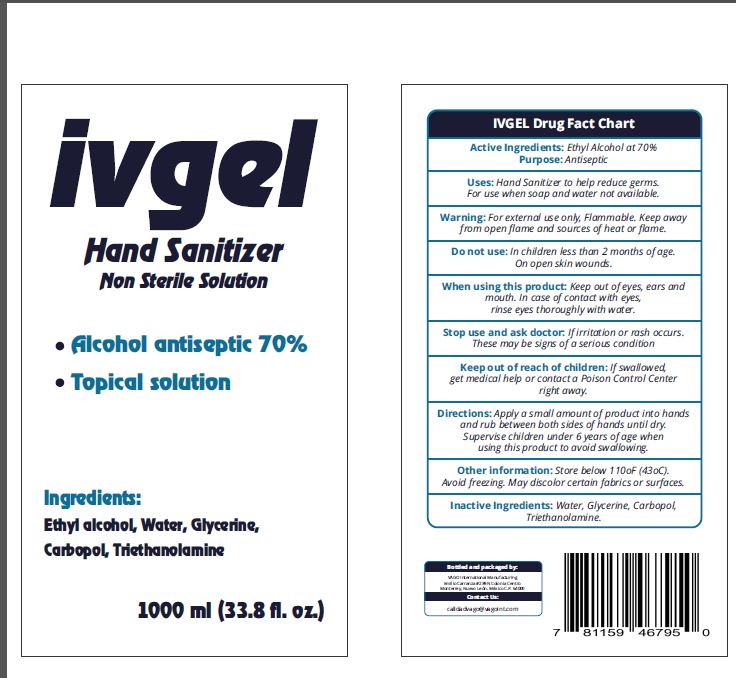 DRUG LABEL: IVGEL Hand Sanitizer
NDC: 74967-000 | Form: GEL
Manufacturer: Vago International Manufacturing SA de CV
Category: otc | Type: HUMAN OTC DRUG LABEL
Date: 20200505

ACTIVE INGREDIENTS: ALCOHOL 0.7 mL/1 mL
INACTIVE INGREDIENTS: WATER; GLYCERIN; CARBOMER HOMOPOLYMER, UNSPECIFIED TYPE; TROLAMINE

IVGEL Hand Sanitizer, 1000mL

Active ingredients:

Ethyl Alcohol at 70%

Purpose

Antiseptic

Uses:

Hand Sanitizer to help reduce germs. For use when soap and water not available.

Warnings:

For external use only, Flammable. Keep away from open flame and sources of heat or flame.

Do not use:

In children lass than 2 months of age. On open skin wounds.

When using this product

Keep out of eyes, ears and mouth. In case of contact with eyes, rinse of serious condition

Stop use and ask doctor:

If a irritation or rash occurs. These may be signs of a serious condition

Keep out of reach of children:

If swallowed, get medical help or contact a Poison Control Center right away.

Directions:

Apply a small amount of product into hands and rub between both side of hands until dry. Supervise children under 6 years of age when
using this product to avoid swallowing.

Other information:

Store below 110oF (43oC). Avoid freezing. May discolor certain fabrics or surface.

Inactive Ingredients:

Water, Glycerin, Carbopol, Trithanolamine